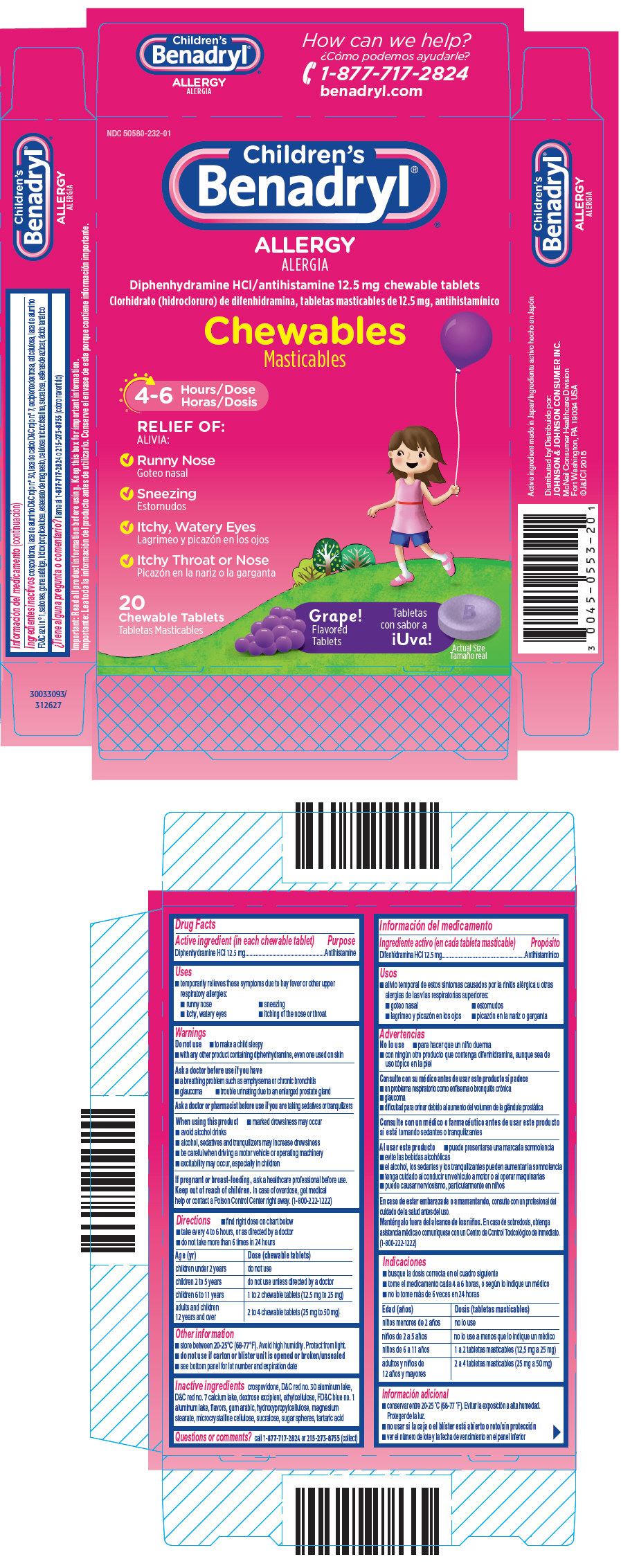 DRUG LABEL: Childrens Benadryl Chewables
NDC: 50580-232 | Form: TABLET, CHEWABLE
Manufacturer: Kenvue Brands LLC
Category: otc | Type: HUMAN OTC DRUG LABEL
Date: 20241108

ACTIVE INGREDIENTS: DIPHENHYDRAMINE HYDROCHLORIDE 12.5 mg/1 1
INACTIVE INGREDIENTS: ALUMINUM OXIDE; D&C RED NO. 7; DEXTROSE, UNSPECIFIED FORM; ETHYLCELLULOSES; FD&C BLUE NO. 1; ACACIA; HYDROXYPROPYL CELLULOSE, UNSPECIFIED; CELLULOSE, MICROCRYSTALLINE; SUCRALOSE; TARTARIC ACID; CROSPOVIDONE; D&C RED NO. 30; MAGNESIUM STEARATE

Children's Benadryl® Chewables

Drug Facts

Active ingredient (in each chewable tablet)

Diphenhydramine HCl 12.5 mg

Purpose

Antihistamine

Uses

- temporarily relieves these symptoms due to hay fever or other upper respiratory allergies:
  - runny nose
  - sneezing
  - itchy, watery eyes
  - itching of the nose or throat

Warnings

Do not use

- to make a child sleepy
- with any other product containing diphenhydramine, even one used on skin

Ask a doctor before use if you have

- a breathing problem such as emphysema or chronic bronchitis
- glaucoma
- trouble urinating due to an enlarged prostate gland

Ask a doctor or pharmacist before use if you are taking sedatives or tranquilizers

When using this product

- marked drowsiness may occur
- avoid alcohol drinks
- alcohol, sedatives and tranquilizers may increase drowsiness
- be careful when driving a motor vehicle or operating machinery
- excitability may occur, especially in children

PREGNANCY OR BREAST FEEDING

If pregnant or breast-feeding, ask a healthcare professional before use.

Keep out of reach of children. In case of overdose, get medical help or contact a Poison Control Center right away. (1-800-222-1222)

Directions

- find right dose on chart below
- take every 4 to 6 hours, or as directed by a doctor
- do not take more than 6 times in 24 hours

Age (yr) | Dose (chewable tablets)
children under 2 years | do not use
children 2 to 5 years | do not use unless directed by a doctor
children 6 to 11 years | 1 to 2 chewable tablets (12.5 mg to 25 mg)
adults and children 12 years and over | 2 to 4 chewable tablets (25 mg to 50 mg)

Other information

- store between 20-25°C (68-77°F). Avoid high humidity. Protect from light.
- do not use if carton or blister unit is opened or broken/unsealed
- see bottom panel for lot number and expiration date

Inactive ingredients

crospovidone, D&C red no. 30 aluminum lake, D&C red no. 7 calcium lake, dextrose excipient, ethylcellulose, FD&C blue no. 1 aluminum lake, flavors, gum arabic, hydroxypropylcellulose, magnesium stearate, microcrystalline cellulose, sucralose, sugar spheres, tartaric acid

Questions or comments?

call 1-877-717-2824 or 215-273-8755 (collect)

PRINCIPAL DISPLAY PANEL

NDC 50580-232-01

Children's
Benadryl®

ALLERGY

Diphenhydramine HCl/antihistamine 12.5 mg chewable tablets

Chewables

4-6 Hours/Dose

RELIEF OF:

- Runny Nose
- Sneezing
- Itchy, Watery Eyes
- Itchy Throat or Nose

20
Chewable Tablets

Grape!
Flavored
Tablets

Actual Size